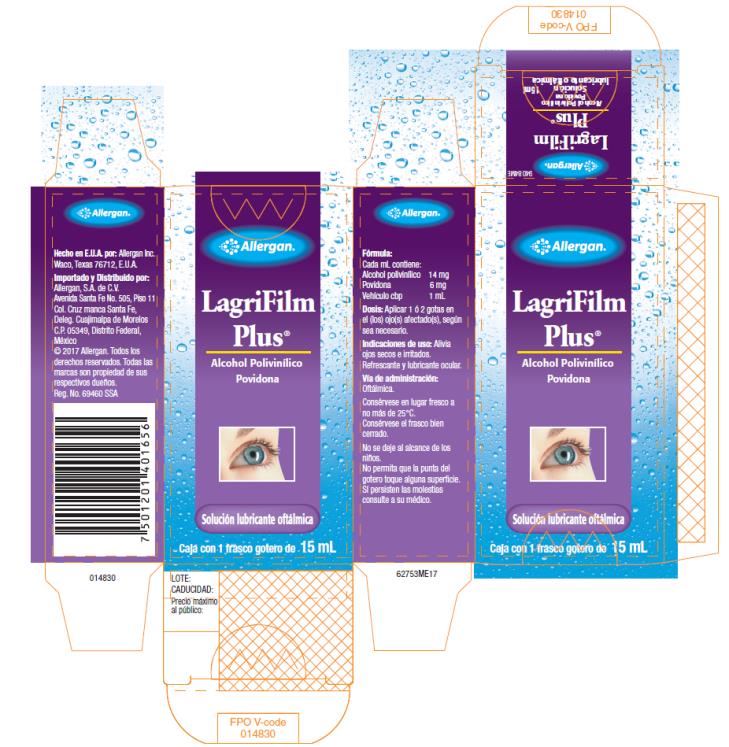 DRUG LABEL: LagriFilm Plus
NDC: 11980-165 | Form: SOLUTION/ DROPS
Manufacturer: Allergan, Inc.
Category: otc | Type: HUMAN OTC DRUG LABEL
Date: 20200211

ACTIVE INGREDIENTS: POLYVINYL ALCOHOL, UNSPECIFIED 14 mg/1 mL; POVIDONE, UNSPECIFIED 6.0 mg/1 mL
INACTIVE INGREDIENTS: SODIUM CHLORIDE 7.8 mg/1 mL; HYDROCHLORIC ACID; SODIUM HYDROXIDE; WATER; CHLOROBUTANOL HEMIHYDRATE 5.25 mg/1 mL

LagriFilm Plus

Principal Display Panel

14 mg/ 6 mg/ 1 mL Carton Label

Allergan®

LagriFilm

Plus®

Alcohol Polivinilico

Povidona

Solucion lubricante oftalmica

Caja con 1 frasco gotero de 15 mL